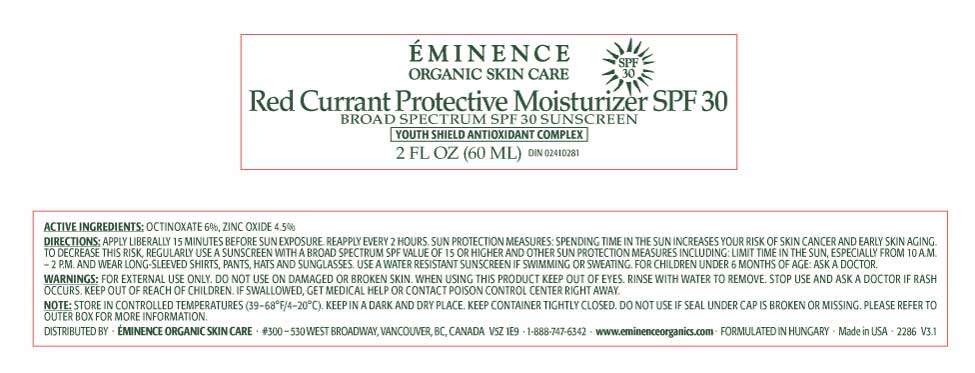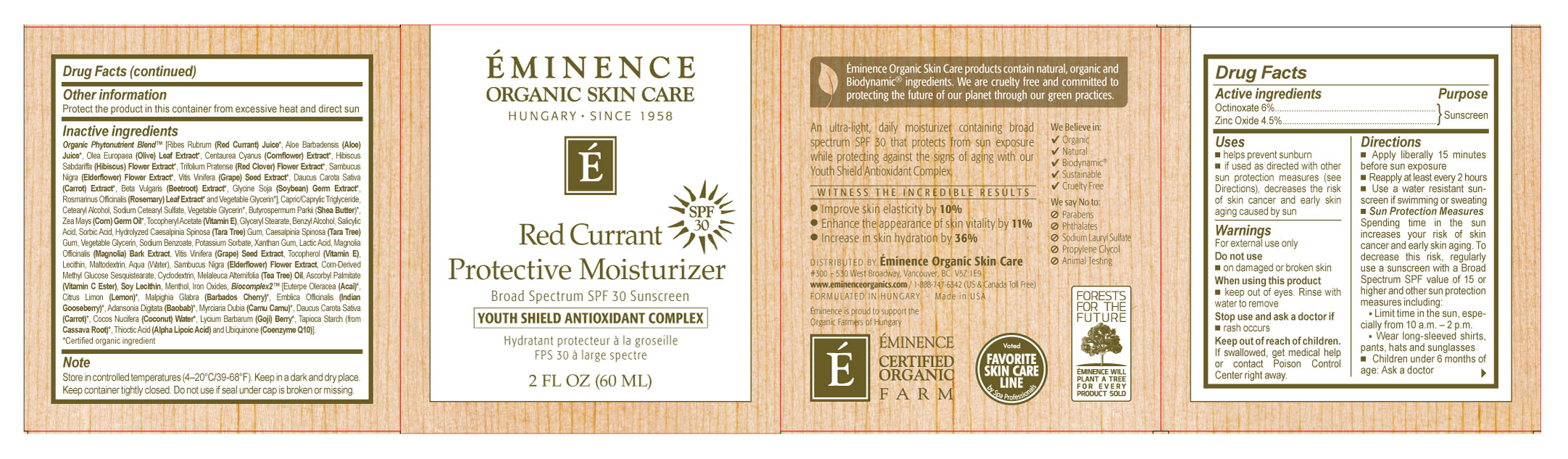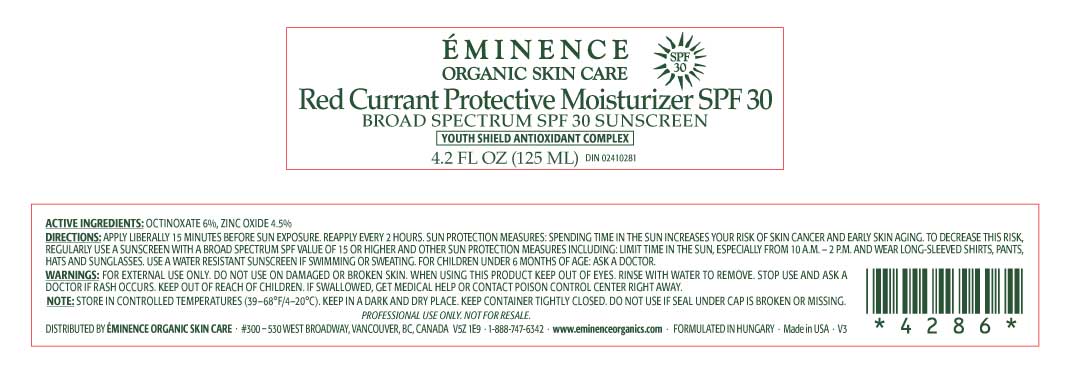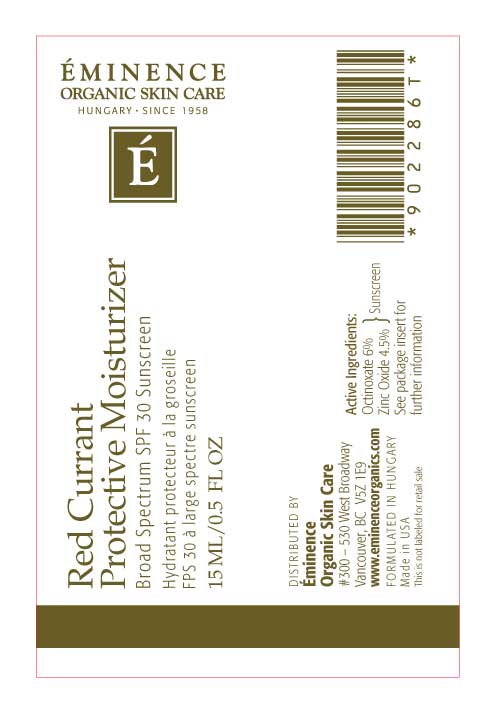 DRUG LABEL: EMINENCE Red Currant Protective Moisturizer
NDC: 15751-2286 | Form: CREAM
Manufacturer: Eminence Organic Skin Care
Category: otc | Type: HUMAN OTC DRUG LABEL
Date: 20251201

ACTIVE INGREDIENTS: OCTINOXATE 60 mg/1 mL; ZINC OXIDE 45 mg/1 mL
INACTIVE INGREDIENTS: SAMBUCUS NIGRA FLOWER; HYDROLYZED WHEAT PROTEIN (ENZYMATIC, 3000 MW); SORBITOL; LYSINE; DIGLYCERIN; LACTIC ACID; GLYCERYL STEARATE SE; PROPANEDIOL; CAPRYLIC/CAPRIC/LAURIC TRIGLYCERIDE; STEARIC ACID; .ALPHA.-TOCOPHEROL ACETATE; RED CURRANT; XANTHAN GUM; VITAMIN A; ASCORBIC ACID; UBIDECARENONE; .ALPHA.-LIPOIC ACID; MODIFIED CORN STARCH (1-OCTENYL SUCCINIC ANHYDRIDE); BEET JUICE; SODIUM SALICYLATE; GRAPE SEED OIL; TOCOPHEROL; MALTODEXTRIN; WATER; MENTHOL; TEA TREE OIL

EMINENCE Red Currant Protective Moisturizer

EMINENCE Red Currant Protective Moisturizer

Drug Facts

Active Ingredients

Octinoxate 6%

Zinc Oxide 4.5%

Purpose

Sunscreen

Uses

- helps prevent sunburn
- if used as directed with other sun protection measures (see), decreases the risk of skin cancer and early skin aging caused by sun Directions

Warnings

For external use only

Do not use

- on damaged or broken skin

When using this product

- keep out of eyes. Rinse with water to remove

Stop use and ask a doctor if

- rash occurs

Keep out of reach of children.

If swallowed, get medical help or contact a Poison Control Center right away.

Directions

- Apply liberally 15 minutes before sun exposure
- Reapply at least every 2 hours
- Use a water resistant sunscreen if swimming or sweating
- Sun Protection Measures
- Spending time in the sun increases your risk of skin cancer and early skin aging. To decrease this risk, regularly use a sunscreen with a Broad Spectrum SPF value of 15 or higher and other sun protection measures including:
- Limit time in the sun, especially from 10 a.m. - 2 p.m/
- Wear long sleeved shirts, pants, hats and sunglasses
- Children under 6 months of age: Ask a doctor

Other Information

Protect the product in this container from excessive heat and direct sun.

Inactive Ingredients

Elderflower Tea, Hydrolyzed Wheat Protein, Sorbitol, Lysine, PCA, Diglycerin, Lactic Acid, Glyceryl Stearate, Propanediol, Coco Caprylate/

Caprate, Caprylic/Capric Triglyceride, Cetyl Stearyl Alcohol, Stearic Acid, Tocopheryl Acetate, Elderflower Extract, Red Currant Extract, Xanthan

Gum, Vitamin A, Vitamin C Ester, Vitamin E, Coenzyme Q10, Alpha Lipoic Acid, Modified Corn Starch, Beet Root Juice, Sodium Salicylate, Magnolia Bark Extract, Grape Seed Extract, Tocopherol, Lecithin, Maltodextrin, Water, Menthol, Elderflower Essence, Microencapsulated Tea Tree Oil.

Distributed By

EMINENCE ORGANIC SKIN CARE 300 – 530 West Broadway Vancouver, BC, Canada V5Z 1E9 www.eminenceorganics.com

MADE IN HUNGARY 1-888-747-6342 (US and Canada Toll Free)

Note:

Store in controlled temperatures (39–68°F/4–20°C). Keep in a dark and dry place. Keep container tightly closed.

Our products contain all organic fruits, vegetables and herbs. They do not contain harmful chemicals or animal by-products. They are not tested on animals and are packaged in environmentally friendly packaging. Do not use if printed seal under cap is broken or missing.